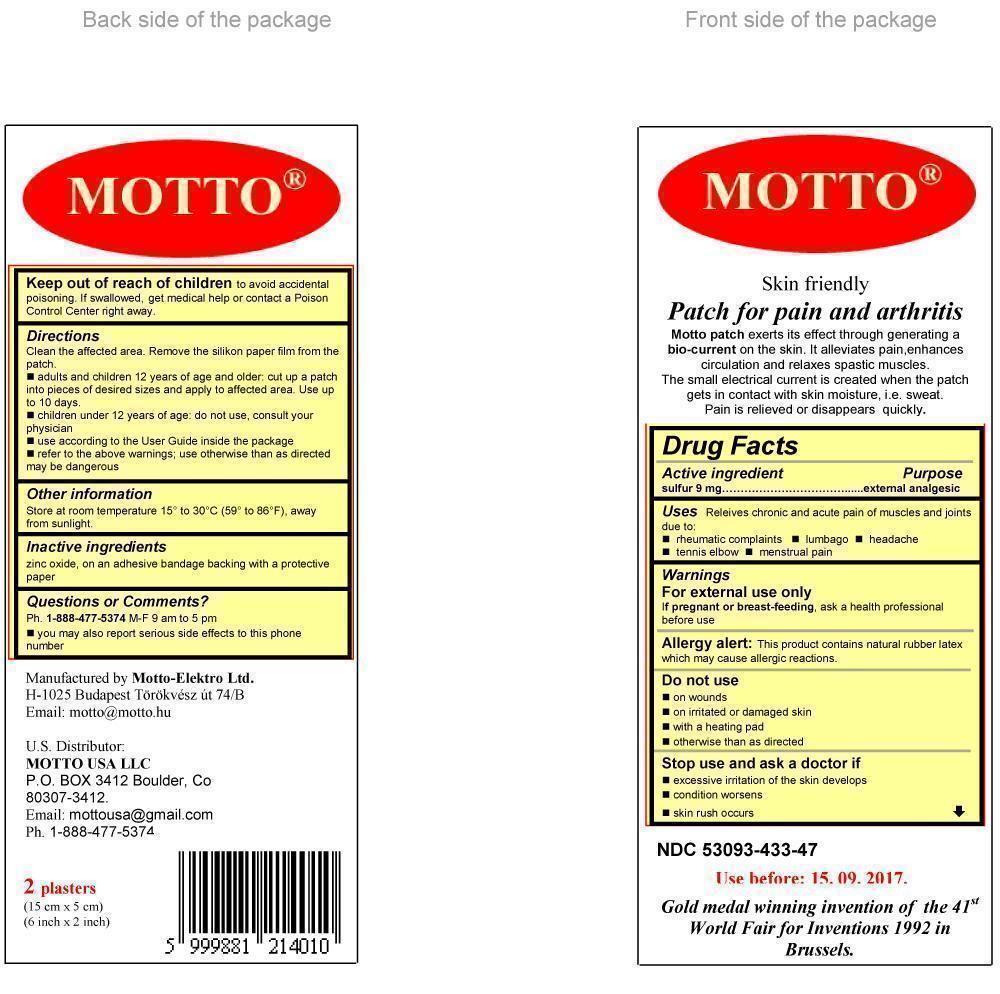 DRUG LABEL: Motto
NDC: 53093-433 | Form: PATCH
Manufacturer: Motto-Elektro Ltd.
Category: otc | Type: HUMAN OTC DRUG LABEL
Date: 20130226

ACTIVE INGREDIENTS: SULFUR 9 mg/9 mg
INACTIVE INGREDIENTS: ZINC OXIDE 3.5 mg/9 mg

Purpose

external analgesic

Uses

Releives chronic and acute pain of muscles and joints due to:

- rheumatic complaints
- lumbago
- headache
- tennis elbow
- menstrual pain

Active ingredient

sulfur 9 mg

Warnings

For external use only

If pregnant or breast-feeding, ask a health professional before use

Allergy alert:

This product contains natural rubber latex which may cause allergic reactions.

Do not use

- on wounds
- on irritated or damaged skin
- with a heating pad
- otherwise than as directed

Stop use and ask a doctor if

- excessive irritation of the skin develops
- condition worsens
- skin rush occurs

Keep out of reach of children

to avoid accidental poisoning. If swallowed, get medical help or contact a Poison Control Center right away.

Directions

Clean the affected area. Remove the silikon paper film from the patch.

Dosage

- adults and children 12 years of age and older: cut up a patch into pieces of desired sizes and apply to affected area. Use up to 10 days.
- children under 12 years of age: do not use, consult your physician
- use according to the User Guide inside the package
- refer to the above warnings; use otherwise than as directed may be dangerous

Other information

Store at room temperature 15° to 30°C (59° to 86°F), away from sunlight.

Inactive ingredient

zinc oxide, on an adhesive bandage backing with a protective paper

Questions or Comments?

Ph. 1-888-477-5374 M-F 9 am to 5 pm

You may also report serious side effects to this phone number.